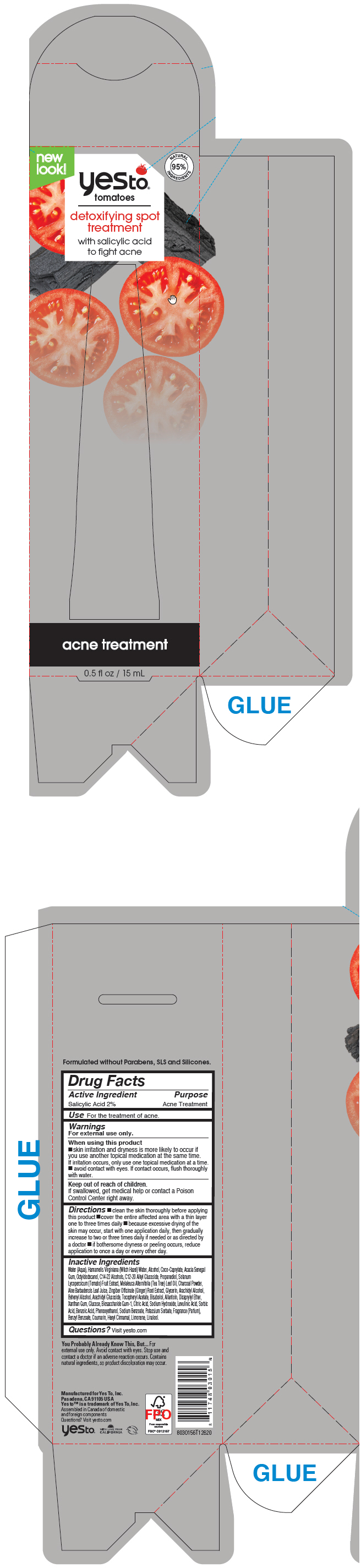 DRUG LABEL: Yes To Tomatoes Detoxifying Spot Treatment
NDC: 69840-026 | Form: LIQUID
Manufacturer: Yes To, Inc.
Category: otc | Type: HUMAN OTC DRUG LABEL
Date: 20210819

ACTIVE INGREDIENTS: SALICYLIC ACID 20 mg/1 mL
INACTIVE INGREDIENTS: ALOE VERA LEAF; WATER; HAMAMELIS VIRGINIANA TOP WATER; PROPANEDIOL; ALLANTOIN; GLYCERIN; ACTIVATED CHARCOAL; SOLANUM LYCOPERSICUM WHOLE; TEA TREE OIL; COCOYL CAPRYLOCAPRATE; ACACIA; OCTYLDODECANOL; XANTHAN GUM; DICAPRYLYL ETHER; C14-22 ALCOHOLS; ARACHIDYL ALCOHOL; BIOSACCHARIDE GUM-1; PHENOXYETHANOL; DOCOSANOL; C12-20 ALKYL GLUCOSIDE; ARACHIDYL GLUCOSIDE; .ALPHA.-TOCOPHEROL ACETATE, DL-; SODIUM HYDROXIDE; .ALPHA.-BISABOLOL, (+/-)-; GINGER; ALCOHOL; ANHYDROUS DEXTROSE; CITRIC ACID MONOHYDRATE; LEVULINIC ACID; SORBIC ACID; BENZOIC ACID; SODIUM BENZOATE; POTASSIUM SORBATE

Yes To® Tomatoes Detoxifying Spot Treatment

Drug Facts

Active Ingredient

Salicylic Acid 2%

Purpose

Acne Treatment

Use

For the treatment of acne.

Warnings

For external use only.

When using this product

- skin irritation and dryness is more likely to occur if you use another topical medication at the same time. If irritation occurs, only use one topical medication at a time.
- avoid contact with eyes. If contact occurs, flush thoroughly with water.

Keep out of reach of children.

If swallowed, get medical help or contact a Poison Control Center right away.

Directions

- clean the skin thoroughly before applying this product
- cover the entire affected area with a thin layer one to three times daily
- because excessive drying of the skin may occur, start with one application daily, then gradually increase to two or three times daily if needed or as directed by a doctor
- if bothersome dryness or peeling occurs, reduce application to once a day or every other day.

Inactive Ingredients

Water (Aqua), Hamamelis Virginiana (Witch Hazel) Water, Alcohol, Coco-Caprylate, Acacia Senegal Gum, Octyldodecanol, C14-22 Alcohols, C12-20 Alkyl Glucoside, Propanediol, Solanum Lycopersicum (Tomato) Fruit Extract, Melaleuca Alternifolia (Tea Tree) Leaf Oil, Charcoal Powder, Aloe Barbadensis Leaf Juice, Zingiber Officinale (Ginger) Root Extract, Glycerin, Arachidyl Alcohol, Behenyl Alcohol, Arachidyl Glucoside, Tocopheryl Acetate, Bisabolol, Allantoin, Dicaprylyl Ether, Xanthan Gum, Glucose, Biosaccharide Gum-1, Citric Acid, Sodium Hydroxide, Levulinic Acid, Sorbic Acid, Benzoic Acid, Phenoxyethanol, Sodium Benzoate, Potassium Sorbate, Fragrance (Parfum), Benzyl Benzoate, Coumarin, Hexyl Cinnamal, Limonene, Linalool.

Questions?

Visit yesto.com

PRINCIPAL DISPLAY PANEL - 15 mL Tube Box

new
look!

NATURAL
95%
INGREDIENTS

yesto®
tomatoes

detoxifying spot
treatment
with salicylic acid
to fight acne

acne treatment

0.5 fl oz / 15 mL